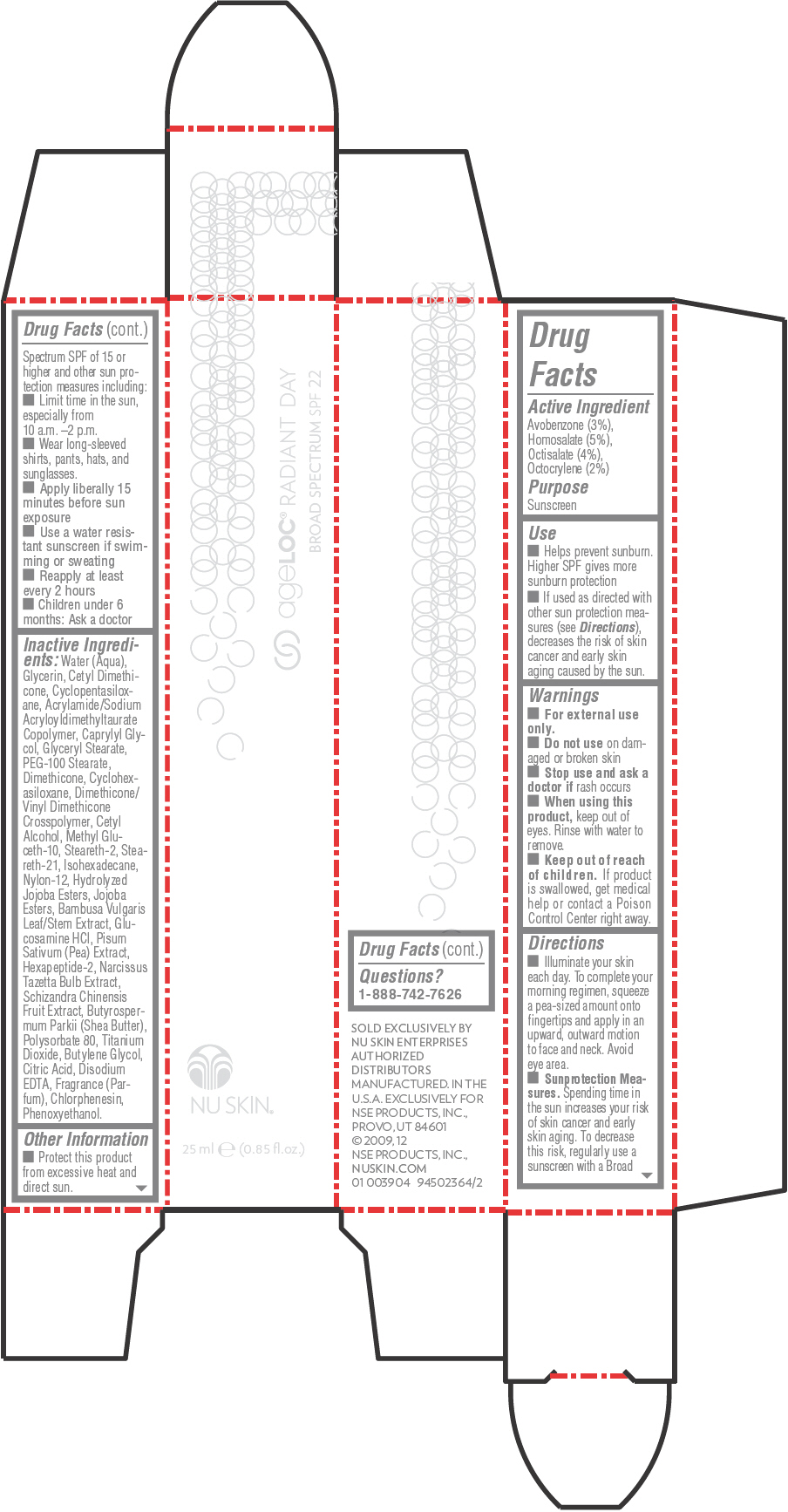 DRUG LABEL: Nu Skin ageLOC Radiant Day Broad Spectrum SPF 22
NDC: 62839-3904 | Form: LOTION
Manufacturer: NSE Products, Inc.
Category: otc | Type: HUMAN OTC DRUG LABEL
Date: 20241227

ACTIVE INGREDIENTS: Avobenzone 30 mg/1 mL; Homosalate 50 mg/1 mL; Octisalate 40 mg/1 mL; Octocrylene 20 mg/1 mL
INACTIVE INGREDIENTS: WATER; GLYCERIN; CYCLOMETHICONE 5; CAPRYLYL GLYCOL; GLYCERYL MONOSTEARATE; PEG-100 STEARATE; CETYL ALCOHOL; METHYL GLUCETH-10; STEARETH-2; STEARETH-21; ISOHEXADECANE; DIMETHICONE; NYLON-12; PHENOXYETHANOL; CHLORPHENESIN; CYCLOMETHICONE 6; POLYSORBATE 80; GLUCOSAMINE HYDROCHLORIDE; SHEA BUTTER; TITANIUM DIOXIDE; PEA; BUTYLENE GLYCOL; EDETATE DISODIUM; BAMBUSA VULGARIS TOP; NARCISSUS TAZETTA BULB; CITRIC ACID MONOHYDRATE; SCHISANDRA CHINENSIS FRUIT

Nu Skin® ageLOC® Radiant Day Broad Spectrum SPF 22

Drug Facts

Active Ingredient

Avobenzone (3%), Homosalate (5%), Octisalate (4%), Octocrylene (2%)

Purpose

Sunscreen

Use

- Helps prevent sunburn. Higher SPF gives more sunburn protection
- If used as directed with other sun protection measures (see Directions), decreases the risk of skin cancer and early skin aging caused by the sun.

Warnings

- For external use only.
- Do not use on damaged or broken skin

- Stop use and ask a doctor if rash occurs

- When using this product, keep out of eyes. Rinse with water to remove.

- Keep out of reach of children. If product is swallowed, get medical help or contact a Poison Control Center right away.

Directions

- Illuminate your skin each day. To complete your morning regimen, squeeze a pea-sized amount onto fingertips and apply in an upward, outward motion to face and neck. Avoid eye area.
- Sunprotection Measures. Spending time in the sun increases your risk of skin cancer and early skin aging. To decrease this risk, regularly use a sunscreen with a Broad Spectrum SPF of 15 or higher and other sun protection measures including:
  - Limit time in the sun, especially from 10 a.m. –2 p.m.
  - Wear long-sleeved shirts, pants, hats, and sunglasses.
  - Apply liberally 15 minutes before sun exposure
  - Use a water resistant sunscreen if swimming or sweating
  - Reapply at least every 2 hours
- Children under 6 months: Ask a doctor

Inactive Ingredients

Water (Aqua), Glycerin, Cetyl Dimethicone, Cyclopentasiloxane, Acrylamide/Sodium Acryloyldimethyltaurate Copolymer, Caprylyl Glycol, Glyceryl Stearate, PEG-100 Stearate, Dimethicone, Cyclohexasiloxane, Dimethicone/ Vinyl Dimethicone Crosspolymer, Cetyl Alcohol, Methyl Gluceth-10, Steareth-2, Steareth-21, Isohexadecane, Nylon-12, Hydrolyzed Jojoba Esters, Jojoba Esters, Bambusa Vulgaris Leaf/Stem Extract, Glucosamine HCl, Pisum Sativum (Pea) Extract, Hexapeptide-2, Narcissus Tazetta Bulb Extract, Schizandra Chinensis Fruit Extract, Butyrospermum Parkii (Shea Butter), Polysorbate 80, Titanium Dioxide, Butylene Glycol, Citric Acid, Disodium EDTA, Fragrance (Parfum), Chlorphenesin, Phenoxyethanol.

Other Information

- Protect this product from excessive heat and direct sun.

Questions?

1-888-742-7626

PRINCIPAL DISPLAY PANEL - 25 ml Tube Carton

ageLOC® RADIANT DAY
BROAD SPECTRUM SPF 22

NU SKIN®

25 ml e (0.85 fl .oz.)